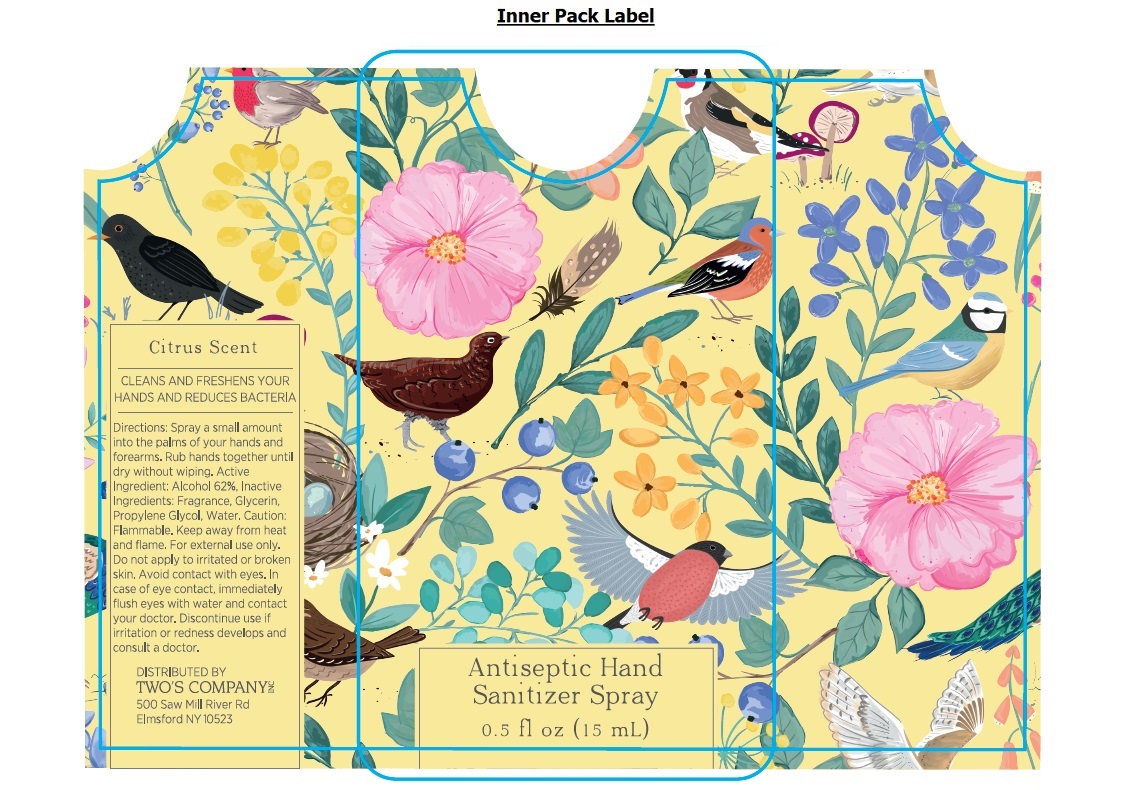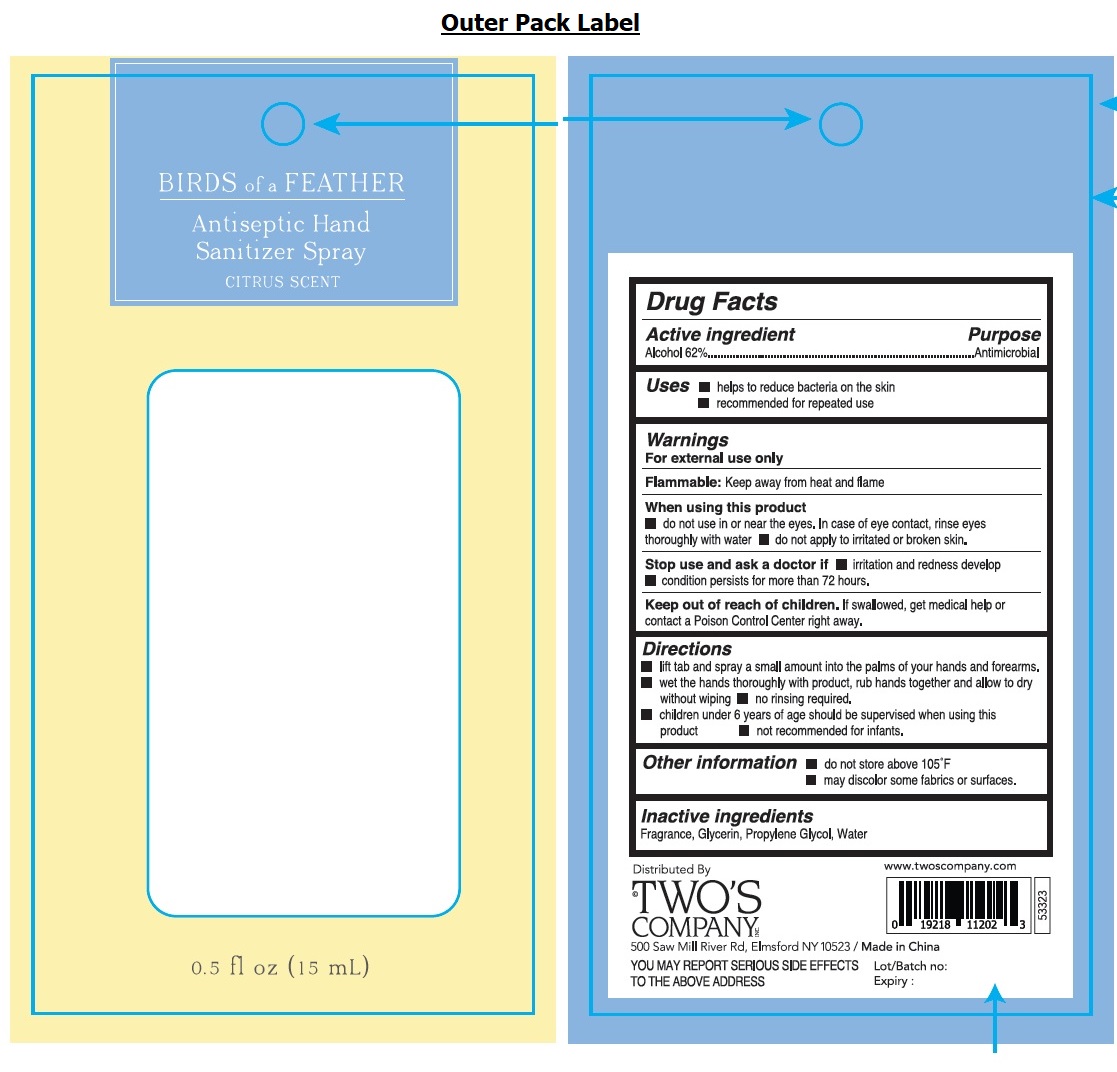 DRUG LABEL: Antiseptic Hand Sanitizer
NDC: 72762-005 | Form: SPRAY
Manufacturer: Two's Company, Inc.
Category: otc | Type: HUMAN OTC DRUG LABEL
Date: 20210618

ACTIVE INGREDIENTS: ALCOHOL 0.62 mL/1 mL
INACTIVE INGREDIENTS: GLYCERIN; PROPYLENE GLYCOL; WATER

BIRDS of a FEATHER Antiseptic Hand Sanitizer Spray CITRUS SCENT

Active ingredient

Alcohol 62%

Purpose

Antimicrobial

INDICATIONS AND USAGE

Uses ■ helps to reduce bacteria on the skin

■ recommended for repeated use

Warnings

For external use only.

Flammable: Keep away from heat and flame

when using this product

■ do not use in or near the eyes. In case of eye contact, rinse eyes thoroughly with water ■ do not apply to irritated or broken skin.

Stop use and ask a doctor if ■ irritation and redness develop ■ condition persists for more than 72 hours.

Keep out of reach of children. If swallowed, get medical help or contact a Poison Control Center right away.

Directions

■ lift tab and spray a small amount into the palms of your hands and forearms.

■ wet the hands thoroughly with product, rub hands together and allow to dry without wiping ■ no rinsing required.

■ children under 6 years of age should be supervised when using this product ■ not recommended for infants.

Other information ■ do not store above 105°F

■ may discolor some fabrics or surfaces.

Inactive ingredients

Fragrance, Glycerin, Propylene Glycol, Water

CLEANS AND FRESHENS YOUR HANDS AND REDUCES BACTERIA

Distributed By

TWO'S COMPANY INC

500 Saw Mill River Rd, Elmsford NY 10523/ Made in China

YOU MAY REPORT SERIOUS SIDE EFFECTS TO THE ABOVE ADDRESS

www.twoscompany.com